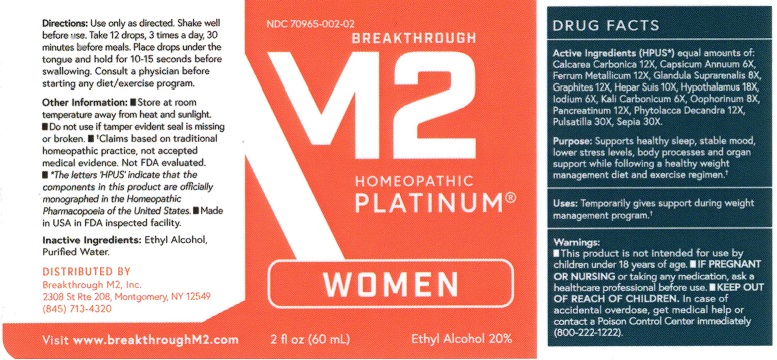 DRUG LABEL: Womens PLATINUM
NDC: 70965-002 | Form: LIQUID
Manufacturer: Breakthrough M2 Inc
Category: homeopathic | Type: HUMAN OTC DRUG LABEL
Date: 20181023

ACTIVE INGREDIENTS: OYSTER SHELL CALCIUM CARBONATE, CRUDE 12 [hp_X]/59 mL; CAPSICUM 6 [hp_X]/59 mL; IRON 12 [hp_X]/59 mL; SUS SCROFA ADRENAL GLAND 8 [hp_X]/59 mL; GRAPHITE 12 [hp_X]/59 mL; PORK LIVER 10 [hp_X]/59 mL; BOS TAURUS HYPOTHALAMUS 18 [hp_X]/59 mL; IODINE 6 [hp_X]/59 mL; POTASSIUM CARBONATE 6 [hp_X]/59 mL; SUS SCROFA OVARY 8 [hp_X]/59 mL; PANCRELIPASE 12 [hp_X]/59 mL; PHYTOLACCA AMERICANA ROOT 12 [hp_X]/59 mL; PULSATILLA VULGARIS 30 [hp_X]/59 mL; SEPIA OFFICINALIS JUICE 30 [hp_X]/59 mL
INACTIVE INGREDIENTS: WATER; ALCOHOL

Breakthrough M2 Women's PLATINUM

Active Ingredients (HPUS*)

equal amounts of: Calcarea Carbonica 12X, Capsicum Annuum 6X, Ferrum Metallicum 12X, Glandula Suprarenalis 8X, Graphites 12X, Hepar Suis 10X, Hypothalamus 18X, Iodium 6X, Kali Carbonicum 6X, Oophorinum 8X, Pancreatinum 12X, Phytolacca Decandra 12X, Pulsatilla 30X, Sepia 30X.

†Claims based on traditional homeopathic practice, not accepted medical evidence. Not FDA evaluated.

*The letters "HPUS" indicate that the componenets in this product are officially monographed in the Homeopathic Pharmacopoeia of the

Unitied Sates.

Uses:

Temporarily gives support during weight management program.†

Warnings

- This product is not intended for use by children under 18 years of age.
- IF PREGNANT OR NURSING or taking any medication, ask a healthcare professional before use.
- KEEP OUT OF REACH OF CHILDERN. In case of accidental overdose, get medical help or contact a Poison Control Center immediately (800-222-1222).

KEEP OUT OF REACH OF CHILDREN.

DOSAGE AND ADMINISTRATION

Directions: Use only as directed. Shake well before use. Take 12 drops, 3 times a day, 30 minutes before meals. Place drops under the tongue and hold for 10-15 seconds before starting any diet/exercise program.

Other information: • Store at room temperature away from heat and sunlight. • Do not use if tamper evident neck seal is missing or broken.

Inactive ingredients:

Ethyl Alcohol, Purified Water

QUESTIONS

Distributed By

Breakthrough M2 Inc.

2308 St. Rte 208, Montgomery, NY 12549

(845) 713-4320

Visit www.breakthroughM2.com

Made in USA in FDA inspected facility.

PACKAGE LABEL

NDC 70965-002-02

Breakthrough

M2

Homeopathic

PLATINUM®

WOMEN

2 fl oz (60 mL)

Ethyl Alcohol 20%

PURPOSE

Purpose: Supports healthy sleep, stable mood, lower stress levels, body processes and organ support while following a healthy weight management diet and exercise regimen.†